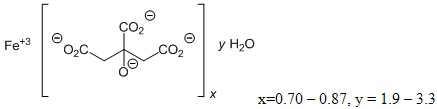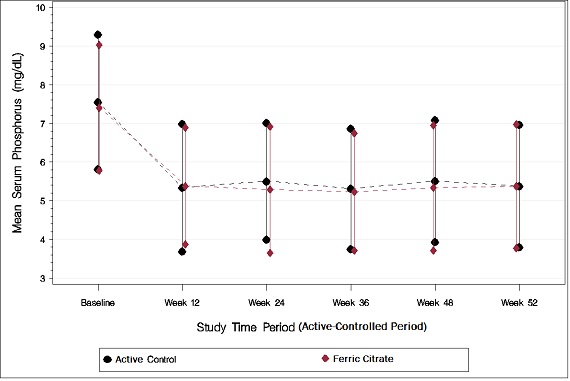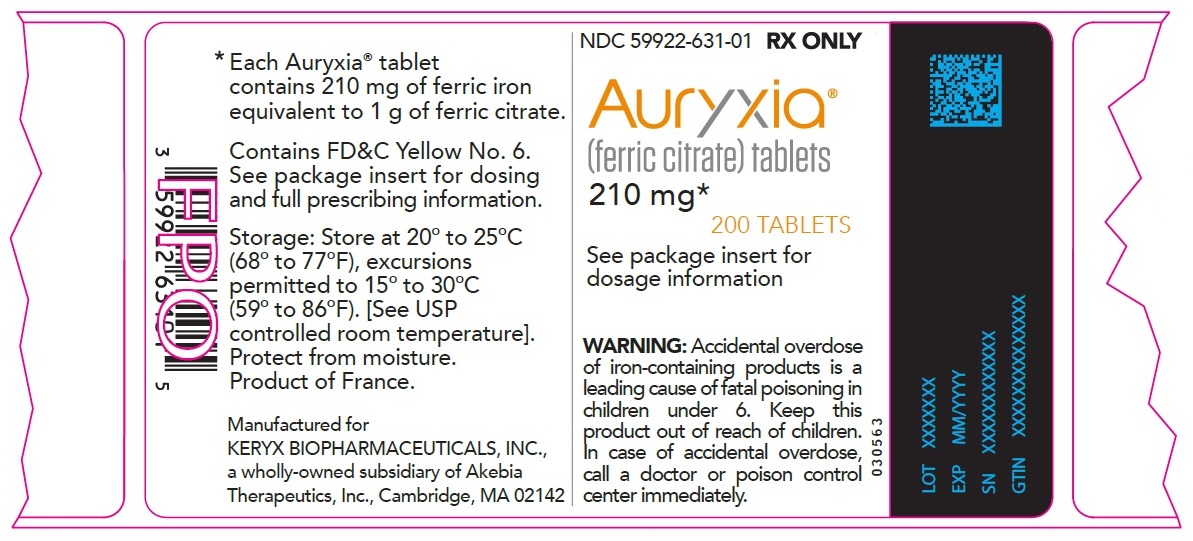 DRUG LABEL: Auryxia
NDC: 59922-631 | Form: TABLET, FILM COATED
Manufacturer: Akebia Therapeutics, Inc.
Category: prescription | Type: HUMAN PRESCRIPTION DRUG LABEL
Date: 20241204

ACTIVE INGREDIENTS: TETRAFERRIC TRICITRATE DECAHYDRATE 210 mg/1 1

HIGHLIGHTS OF PRESCRIBING INFORMATION

These highlights do not include all the information needed to use AURYXIA® safely and effectively. See full prescribing information for AURYXIA.
AURYXIA (ferric citrate) tablets, for oral use
Initial U.S. Approval: 2014

1 INDICATIONS AND USAGE

Auryxia is a phosphate binder indicated for the control of serum phosphorus levels in adult patients with chronic kidney disease on dialysis. (1)

Auryxia is an iron replacement product indicated for the treatment of iron deficiency anemia in adult patients with chronic kidney disease not on dialysis. (1)

2 DOSAGE AND ADMINISTRATION

- Hyperphosphatemia in Chronic Kidney Disease on Dialysis:
  - Starting dose is 2 tablets orally 3 times per day with meals. (2.1)
  - Adjust dose by 1 to 2 tablets as needed to maintain serum phosphorus at target levels, up to a maximum of 12 tablets daily. Dose can be titrated at 1-week or longer intervals. (2.1)
- Iron Deficiency Anemia in Chronic Kidney Disease Not on Dialysis:
  - Starting dose is 1 tablet orally 3 times per day with meals. (2.2)
  - Adjust dose as needed to achieve and maintain hemoglobin goal, up to a maximum of 12 tablets daily. (2.2)

3 DOSAGE FORMS AND STRENGTHS

- Tablets: 210 mg ferric iron, equivalent to 1 g ferric citrate. (3)

4 CONTRAINDICATIONS

- Iron overload syndromes (e.g., hemochromatosis). (4)

5 WARNINGS AND PRECAUTIONS

- Iron overload: Monitor ferritin and TSAT. Patients may require a reduction in dose or discontinuation of intravenous iron. (5.1)
- Accidental overdose of iron-containing products is a leading cause of fatal poisoning in children under 6 years of age. Keep this product out of reach of children. In case of accidental overdose, call a doctor or poison control center immediately. (5.2)

6 ADVERSE REACTIONS

Most common adverse reactions (incidence ≥5%) are discolored feces, diarrhea, constipation, nausea, vomiting, cough, abdominal pain, and hyperkalemia. (6.1)

To report SUSPECTED ADVERSE REACTIONS, contact Keryx Biopharmaceuticals at 1-844-445-3799 or FDA at 1-800-FDA-1088 or www.fda.gov/medwatch

7 DRUG INTERACTIONS

When clinically significant drug interactions are expected, consider separation of the timing of administration. Consider monitoring clinical responses or blood levels of the concomitant medication. (7)

FULL PRESCRIBING INFORMATION

1 INDICATIONS AND USAGE

1.1 Hyperphosphatemia in Chronic Kidney Disease on Dialysis

Auryxia is indicated for the control of serum phosphorus levels in adult patients with chronic kidney disease on dialysis.

1.2 Iron Deficiency Anemia in Chronic Kidney Disease Not on Dialysis

Auryxia is indicated for the treatment of iron deficiency anemia in adult patients with chronic kidney disease not on dialysis.

2 DOSAGE AND ADMINISTRATION

2.1 Dosage for Hyperphosphatemia in Chronic Kidney Disease on Dialysis

The recommended starting dose is 2 tablets, swallowed whole, 3 times per day with meals. Auryxia tablets must not be chewed or crushed because it may cause discoloration of mouth and teeth. Monitor serum phosphorus levels and titrate the Auryxia dose in decrements or increments of 1 to 2 tablets per day as needed to maintain serum phosphorus at target levels, up to a maximum dose of 12 tablets daily. Dose can be titrated at 1-week or longer intervals.

In a clinical trial, patients required an average of 8 to 9 tablets a day to control serum phosphorus levels.

2.2 Dosage for Iron Deficiency Anemia in Chronic Kidney Disease Not on Dialysis

The recommended starting dose is 1 tablet, swallowed whole, 3 times per day with meals. Auryxia tablets must not be chewed or crushed because it may cause discoloration of mouth and teeth. Titrate the dose of Auryxia as needed to achieve and maintain hemoglobin at target levels, up to a maximum dose of 12 tablets daily.

In a clinical trial in patients with chronic kidney disease not on dialysis (CKD-NDD), patients required an average of 5 tablets per day to increase hemoglobin levels.

3 DOSAGE FORMS AND STRENGTHS

Tablets: Auryxia 210 mg ferric iron, equivalent to 1 g ferric citrate, film-coated, peach-colored, and oval-shaped tablet debossed with “KX52.”

4 CONTRAINDICATIONS

Auryxia is contraindicated in patients with iron overload syndromes (e.g., hemochromatosis) [see Warnings and Precautions (5.1)].

5 WARNINGS AND PRECAUTIONS

5.1 Iron Overload

Iron absorption from Auryxia may lead to excessive elevations in iron stores. Increases in serum ferritin and transferrin saturation (TSAT) levels were observed in clinical trials. In a 56-week safety and efficacy trial evaluating the control of serum phosphate levels in patients with chronic kidney disease on dialysis in which concomitant use of intravenous iron was permitted, 55 (19%) of patients treated with Auryxia had a ferritin level >1500 ng/mL as compared with 13 (9%) of patients treated with active control.

Assess iron parameters (e.g., serum ferritin and TSAT) prior to initiating Auryxia and monitor iron parameters while on therapy [see Contraindications (4), Overdosage (10) and Clinical Pharmacology (12.2)]. Patients receiving intravenous iron may require a reduction in dose or discontinuation of intravenous iron therapy.

5.2 Risk of Overdosage in Children Due to Accidental Ingestion

Accidental ingestion and resulting overdose of iron-containing products is a leading cause of fatal poisoning in children under 6 years of age [see Overdosage (10)]. Advise patients of the risks to children and to keep Auryxia out of the reach of children.

6 ADVERSE REACTIONS

6.1 Clinical Trials Experience

Because clinical trials are conducted under widely varying conditions, adverse reaction rates observed in the clinical trials of a drug cannot be directly compared to adverse reaction rates in the clinical trials of another drug and may not reflect the rates observed in practice.

Hyperphosphatemia in Chronic Kidney Disease on Dialysis

A total of 289 patients were treated with Auryxia and 149 patients were treated with active control (sevelamer carbonate and/or calcium acetate) during the 52-week, randomized, open-label, active control phase of a trial in patients on dialysis. A total of 322 patients were treated with Auryxia for up to 28 days in three short-term trials. Across these trials, 557 unique patients were treated with Auryxia; dosage regimens in these trials ranged from 210 mg to 2,520 mg of ferric iron per day, equivalent to 1 to 12 tablets of Auryxia.

Adverse reactions reported in more than 5% of patients treated with Auryxia in these trials included diarrhea (21%), discolored feces (19%), nausea (11%), constipation (8%), vomiting (7%), and cough (6%).

During the 52-week, active-control period, 61 patients (21%) on Auryxia discontinued study drug because of an adverse reaction, as compared to 21 patients (14%) in the active control arm. Patients who were previously intolerant to any of the active control treatments (calcium acetate and sevelamer carbonate) were not eligible to enroll in the study. Gastrointestinal adverse reactions were the most common reason for discontinuing Auryxia (14%).

Iron Deficiency Anemia in Chronic Kidney Disease Not on Dialysis

Across two trials, 190 patients with CKD-NDD were treated with Auryxia. This included a study of 117 patients treated with Auryxia and 116 patients treated with placebo in a 16-week, randomized, double-blind period and a study of 75 patients treated with Auryxia and 73 treated with placebo in a 12-week randomized double-blind period. Dosage regimens in these trials ranged from 210 mg to 2,520 mg of ferric iron per day, equivalent to 1 to 12 tablets of Auryxia.

Adverse reactions reported in at least 5% of patients treated with Auryxia in these trials are listed in Table 1.

Table 1: Adverse Events Reported in Two Clinical Trials in at least 5% of patients receiving Auryxia
Body System Adverse Reaction | Auryxia % (N=190) | Placebo % (N=188)
Any Adverse Reaction | 75 | 62
Metabolism and Nutrition Disorders
Hyperkalemia | 5 | 3
Gastrointestinal Disorders
Discolored feces | 22 | 0
Diarrhea | 21 | 12
Constipation | 18 | 10
Nausea | 10 | 4
Abdominal Pain | 5 | 2

During the 16-week, placebo-control trial, 12 patients (10%) on Auryxia discontinued study drug because of an adverse reaction, as compared to 10 patients (9%) in the placebo control arm. Diarrhea was the most common adverse reaction leading to discontinuation of Auryxia (2.6%).

7 DRUG INTERACTIONS

Table 2:
Oral drugs that can be administered concomitantly with Auryxia
Amlodipine Aspirin Atorvastatin Calcitriol Clopidogrel Digoxin Diltiazem Doxercalciferol Enalapril Fluvastatin Glimepiride Levofloxacin Losartan | Metoprolol Pravastatin Propranolol Sitagliptin Warfarin
Oral drugs that have to be separated from Auryxia and meals
 | Dosing Recommendations
Doxycycline | Take at least 1 hour before Auryxia
Ciprofloxacin | Take at least 2 hours before or after Auryxia

Oral medications not listed in Table 2

There are no empirical data on avoiding drug interactions between Auryxia and most concomitant oral drugs. For oral medications where a reduction in the bioavailability of that medication would have a clinically significant effect on its safety or efficacy, consider separation of the timing of the administration of the two drugs. The duration of separation depends upon the absorption characteristics of the medication concomitantly administered, such as the time to reach peak systemic levels and whether the drug is an immediate release or an extended release product. Consider monitoring clinical responses or blood levels of concomitant medications that have a narrow therapeutic range.

8 USE IN SPECIFIC POPULATIONS

8.1 Pregnancy

Risk Summary

There are no available data on Auryxia use in pregnant women to inform a drug-associated risk of major birth defects and miscarriage. Animal reproduction studies have not been conducted using Auryxia. Skeletal and encephalic malformation was observed in neonatal mice when ferric gluconate was administered intraperitoneally to gravid dams on gestation days 7-9. However, oral administration of other ferric or ferrous compounds to gravid CD1-mice and Wistar-rats caused no fetal malformation.

An overdose of iron in pregnant women may carry a risk for spontaneous abortion, gestational diabetes and fetal malformation.

The estimated background risk of major birth defects and miscarriage for the indicated population is unknown. Adverse outcomes in pregnancy occur regardless of the health of the mother or the use of medications. In the U.S. general population, the estimated background risks of major birth defects and miscarriage in clinically recognized pregnancies are 2 to 4% and 15 to 20%, respectively.

Clinical Considerations

The effect of Auryxia on the absorption of vitamins and other nutrients has not been studied in pregnant women. Requirements for vitamins and other nutrients are increased in pregnancy.

8.2 Lactation

Risk Summary

There are no human data regarding the effect of Auryxia in human milk, the effects on the breastfed child, or the effects on milk production. Data from rat studies have shown the transfer of iron into milk by divalent metal transporter-1 (DMT-1) and ferroportin-1 (FPN-1). Hence, there is a possibility of infant exposure when Auryxia is administered to a nursing woman. The development and health benefits of breastfeeding should be considered along with the mother’s clinical need for Auryxia and any potential adverse effects on the breastfed child from Auryxia or from the underlying maternal condition.

8.4 Pediatric Use

The safety and efficacy of Auryxia have not been established in pediatric patients.

Juvenile Animal Toxicity Data

In animal studies, greater gastrointestinal toxicity was observed when ferric citrate was administered by gavage as compared to administration with solid food. Because Auryxia is recommended to be taken with meals and patients under 6 months of age are unlikely to be eating solid food, they may be at greater risk of gastrointestinal toxicity.

8.5 Geriatric Use

Clinical studies of Auryxia included 292 subjects aged 65 years and older (104 subjects aged 75 years and older). Overall, the clinical study experience has not identified any obvious differences in responses between the elderly and younger patients in the tolerability or efficacy of Auryxia.

10 OVERDOSAGE

No data are available regarding overdose of Auryxia in patients. In patients with chronic kidney disease, the maximum dose studied was 2,520 mg ferric iron (12 tablets of Auryxia) per day. Iron absorption from Auryxia may lead to excessive elevations in iron stores, especially when concomitant intravenous iron is used [see Warnings and Precautions (5.1)].

In clinical trials, one case of elevated iron in the liver as confirmed by biopsy was reported in a patient on dialysis administered intravenous iron and Auryxia.

11 DESCRIPTION

Auryxia (ferric citrate), a phosphate binder and iron replacement product, is known chemically as iron (+3), x (1, 2, 3-propanetricarboxylic acid, 2 hydroxy-), y (H2O)

Auryxia 210 mg ferric iron tablets for oral administration, equivalent to 1g ferric citrate, are film-coated, peach-colored, and oval-shaped tablets debossed with “KX52.” The inactive ingredients are pregelatinized starch and calcium stearate. In addition, the film-coating contains the following inactive ingredients: hypromellose, titanium dioxide, triacetin, and FD&C Yellow #6/Sunset Yellow FCF Aluminum Lake, FD&C Red #40/Allura Red AC Aluminum Lake, and FD&C Blue #2/Indigo Carmine Aluminum Lake.

12 CLINICAL PHARMACOLOGY

12.1 Mechanism of Action

Hyperphosphatemia in Chronic Kidney Disease on Dialysis

Ferric iron binds dietary phosphate in the GI tract and precipitates as ferric phosphate. This compound is insoluble and is excreted in the stool. By binding phosphate in the GI tract and decreasing absorption, ferric citrate lowers the phosphate concentration in the serum.

Iron Deficiency Anemia in Chronic Kidney Disease Not on Dialysis

Ferric iron is reduced from the ferric to the ferrous form by ferric reductase in the GI tract. After transport through the enterocytes into the blood, oxidized ferric iron circulates bound to the plasma protein transferrin, and can be incorporated into hemoglobin.

12.2 Pharmacodynamics

Hyperphosphatemia in Chronic Kidney Disease on Dialysis

Auryxia reduces serum phosphorus levels and has also been shown to increase serum iron parameters, including ferritin, iron and TSAT. In dialysis patients treated with Auryxia for hyperphosphatemia in a 52-week study in which intravenous iron could also be administered, mean (SD) ferritin levels rose from 593 (293) ng/mL to 895 (482) ng/mL, mean (SD) TSAT levels rose from 31% (11) to 39% (17) and mean (SD) iron levels rose from 73 (29) mcg/dL to 88 (42) mcg/dL. In contrast, in patients treated with active control, these parameters remained relatively constant [see Contraindications (4) and Warnings and Precautions (5.1)].

Iron Deficiency Anemia in Chronic Kidney Disease Not on Dialysis

Auryxia may increase hemoglobin levels and has also been shown to reduce serum phosphorus levels. In chronic kidney disease patients not on dialysis treated with Auryxia for iron deficiency anemia in a 16-week placebo-controlled study, mean (SD) phosphorus levels decreased from 4.23 (0.91) mg/dL at baseline to 3.72 (0.60) mg/dL. In comparison, in patients treated with placebo control, mean (SD) phosphorus levels decreased from 4.12 (0.68) mg/dL at baseline to 3.87 (0.68) mg/dL.

12.3 Pharmacokinetics

Absorption and Distribution

Formal pharmacokinetic studies have not been performed with Auryxia. Examination of serum iron parameters has shown that there is systemic absorption of iron from Auryxia [see Contraindications (4), Warnings and Precautions (5.1) and Clinical Pharmacology (12.2)].

Drug Interaction Studies

In vitro

Of the drugs screened for an interaction with ferric citrate in vitro, only doxycycline showed the potential for interaction with at least 70% decrease in its concentration. This interaction can be avoided by spacing the administration of doxycycline and ferric citrate [see Drug Interactions (7)].

In vivo

Six drug interaction studies (N=26-60/study) were conducted to establish the effects of Auryxia (administered as 3 x 2 g/day with meals) on the disposition of concomitantly orally administered clopidogrel, ciprofloxacin, digoxin, diltiazem, glimepiride and losartan in healthy subjects. With the exception of ciprofloxacin, Auryxia did not alter the systemic exposure of the tested drugs, as measured by the area under the curve (AUC) and Cmax of the tested drugs when either co-administered with Auryxia or given 2 hours later. Auryxia decreased the relative bioavailability of concomitantly administered ciprofloxacin by approximately 45%. However, there was no interaction when Auryxia and ciprofloxacin were taken 2 hours apart. Consequently, ciprofloxacin should be taken at least 2 hours before or after Auryxia is dosed [see Drug Interactions (7)].

13 NONCLINICAL TOXICOLOGY

13.1 Carcinogenesis, Mutagenesis, Impairment of Fertility

Data from carcinogenesis studies have shown that ferric citrate is not carcinogenic in mice and rats when administered intramuscularly or subcutaneously. Ferric citrate was neither mutagenic in the bacterial reverse mutation assay (Ames test) nor clastogenic in the chromosomal aberration test in Chinese hamster fibroblasts.

The potential for ferric citrate to impair reproductive performance or to cause fetal malformation has not been evaluated.

14 CLINICAL STUDIES

14.1 Hyperphosphatemia in Chronic Kidney Disease on Dialysis

The ability of Auryxia to lower serum phosphorus in patients with CKD on dialysis was demonstrated in randomized clinical trials: one 56-week, safety and efficacy trial, consisting of a 52-week active-controlled phase and a 4-week, placebo-controlled, randomized withdrawal period, and one 4-week open-label trial of different fixed doses of Auryxia. Both trials excluded subjects who had an absolute requirement for aluminum containing drugs with meals.

Study KRX-0502-304 (NCT 01191255)

Study KRX-0502-304 was a long-term, randomized, controlled, safety and efficacy trial. After the 2-week washout period during which phosphate binders were held, patients with a mean serum phosphorus of 7.5 mg/dL during washout were randomized 2:1 to Auryxia (N=292) or active control (calcium acetate and/or sevelamer carbonate; N=149). The majority (>96%) of subjects were on hemodialysis. The starting dose of Auryxia was 6 tablets/day, divided with meals. The starting dose of active control was the patient’s dose prior to the washout period. The dose of phosphate binder was increased or decreased as needed to maintain serum phosphorus levels between 3.5 and 5.5 mg/dL, to a maximum of 12 tablets/day.

As shown in the figure below, serum phosphorus levels declined following initiation of therapy. The phosphorus lowering effect was maintained over 52 weeks of treatment.

Figure 1: Serum Phosphorus Control over 52 Weeks

Following completion of the 52-week active-controlled phase, Auryxia-treated patients were eligible to enter a 4-week placebo-controlled randomized withdrawal phase, in which patients were re-randomized in a 1:1 ratio to receive Auryxia (N=96) or placebo (N=96). During the placebo-controlled period, the serum phosphorus concentration rose by 2.2 mg/dL on placebo relative to patients who remained on Auryxia.

Table 3: Effect of Auryxia on serum phosphorus during randomized withdrawal
Primary Endpoint (Week 56) | Auryxia | Placebo | Treatment Difference (95% CI) | p-value
Serum phosphorus (mg/dL)
Mean baseline (Week 52) | 5.12 | 5.44
Mean change from baseline (Week 56) | -0.24 | 1.79 | −2.18 (−2.59, −1.77) | <0.0001a
a The LS mean treatment difference and p-value for the change in mean were created via an ANCOVA model with treatment as the fixed effect and Week-52 baseline (phosphorus) as the covariate. Between-treatment differences were calculated as the LS mean (Auryxia) - LS mean (placebo or active control).
Note: Analyses using ANCOVA with last observation carried forward. ANCOVA=analysis of covariance; CI=confidence interval.

Study KRX-0502-305 (NCT 01074125)

Following a 1- to 2-week washout from all phosphate-binding agents, 154 patients with hyperphosphatemia (mean serum phosphorus of 7.5 mg/dL) and CKD on dialysis were randomized in a 1:1:1 ratio to 1, 6, or 8 tablets/day of Auryxia for 4 weeks. Auryxia was administered with meals; subjects receiving 1 tablet/day were instructed to take it with their largest meal of the day, and subjects on 6 or 8 tablets/day took divided doses in any distribution with meals. Dose-dependent decreases in serum phosphorus were observed by Day 7 and remained relatively stable for the duration of treatment. The demonstrated reductions from baseline to Week 4 in mean serum phosphorus were significantly greater with 6 and 8 tablets/day than with 1 tablet/day (p<0.0001). Mean reduction in serum phosphorus at Week 4 was 0.1 mg/dL with 1 tablet/day, 1.9 mg/dL with 6 tablets/day, and 2.1 mg/dL with 8 tablets/day.

14.2 Iron Deficiency Anemia in Chronic Kidney Disease Not on Dialysis

Study KRX-0502-306 (NCT 02268994)

The efficacy of Auryxia for the treatment of iron deficiency anemia in adult patients with CKD not on dialysis was demonstrated in a 24-week study consisting of a 16-week, randomized, double-blind, placebo-controlled, efficacy period followed by an 8-week open-label safety extension period in which all patients remaining in the study, including the placebo group, received Auryxia. Patients with eGFR <60 mL/min/1.73m^2, who were intolerant of or have had an inadequate therapeutic response to oral iron supplements, with Hgb ≥9.0 g/dL and ≤11.5 g/dL, serum ferritin ≤200 ng/mL and TSAT ≤25% were enrolled. Patients were randomized to treatment with either Auryxia (n=117) or placebo (n= 117). Dosing with Auryxia or placebo was initiated at 3 tablets/day with meals. Dose titration could occur at Weeks 4, 8 and 12 during Randomized Period, and at Weeks 18 and 20 during Safety Extension Period based on Hgb response. Use of oral or intravenous iron, erythropoiesis stimulating agents (ESAs) was not permitted at any time during the study.

The mean age of the patients was 65 years (range 26 to 93); 63% were female, 69% Caucasian, 30% were African American and <2% were other races.

The main efficacy outcome measure was the proportion of subjects achieving an increase in Hgb of ≥1.0 g/dL at any time point between baseline and the end of the 16-week Randomized Period.

Table 4: Efficacy of Auryxia in Iron Deficiency Anemia in Chronic Kidney Disease (Not on Dialysis)
 | Auryxia (N=117) | Placebo (N=115) | p-value
Proportion of patients achieving an increase in hemoglobin of ≥ 1.0 g/dL at any time point during the 16 week randomized period | 52% | 19% | <0.001

During the 16-week randomized period 49% of subjects in the Auryxia arm and 15% of subjects in the placebo arm (p <0.001) had a mean change in hemoglobin from baseline ≥0.75 g/dL over any 4-week time period provided that an increase of at least 1.0 g/dL had occurred during that 4-week period. Increases in mean hemoglobin (0.75 ± 0.09 g/dL), serum ferritin (163 ± 9 ng/mL) and transferrin saturation (18 ± 1%) were observed from baseline during the 16-week randomized period in the Auryxia arm.

16 HOW SUPPLIED/STORAGE AND HANDLING

16.1 How Supplied

Tablets: Auryxia 210 mg ferric iron tablets equivalent to 1 g of ferric citrate are supplied as 200 tablets in 400cc high-density polyethylene bottles. The 210 mg ferric iron tablets are film-coated, peach-colored, and oval-shaped tablets debossed with “KX52.”

1 Bottle of 200-count 210 mg ferric iron tablets (NDC 59922-631-01)

16.2 Storage and Handling

Storage: Store at 20° to 25°C (68° to 77°F), excursions permitted to 15° to 30°C (59° to 86°F). [See USP controlled room temperature]. Protect from moisture.

17 PATIENT COUNSELING INFORMATION

Dosing Recommendations

Instruct patients to take Auryxia as directed with meals and adhere to their prescribed diets. Instruct patients on concomitant medications that should be dosed apart from Auryxia [see Dosage and Administration (2)]. Instruct patients to swallow the tablets whole, not to chew or crush Auryxia because it may cause discoloration of mouth and teeth.

Adverse Reactions

Advise patients that Auryxia may cause discolored (dark) stools, but this staining of the stool is considered normal with oral medications containing iron.

Auryxia may cause diarrhea, nausea, constipation, vomiting, hyperkalemia, abdominal pain, and cough. Advise patients to report severe or persistent gastrointestinal symptoms to their physician [see Adverse Reactions (6.1)].

Accidental Ingestion

Advise patients to keep this product out of the reach of children and to seek immediate medical attention in case of accidental ingestion by a child.

Manufactured for:

KERYX BIOPHARMACEUTICALS, INC.,
a wholly-owned subsidiary of Akebia Therapeutics, Inc.,
Cambridge, MA 02142

Issued 01/2024 Rev 8.0

PACKAGE LABEL

PRINCIPAL DISPLAY PANEL - NDC: 59922-631-01 - 210 mg 200-ct Bottle